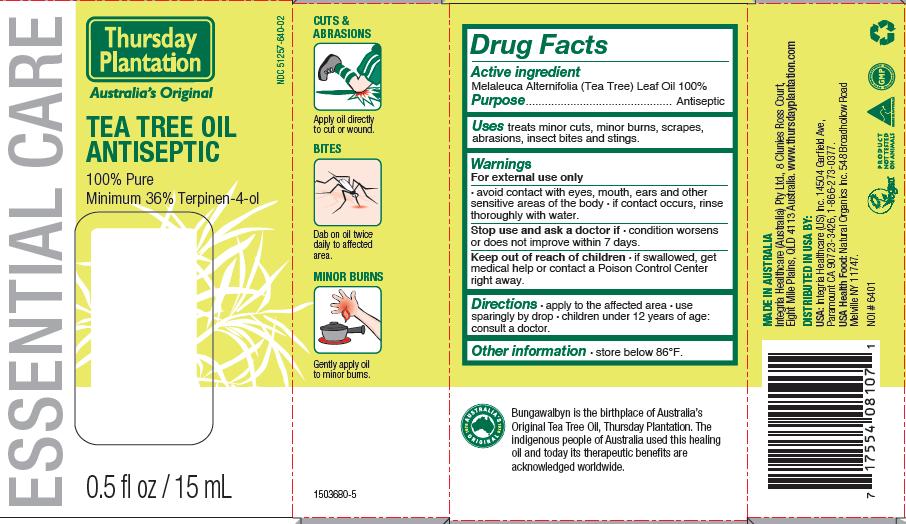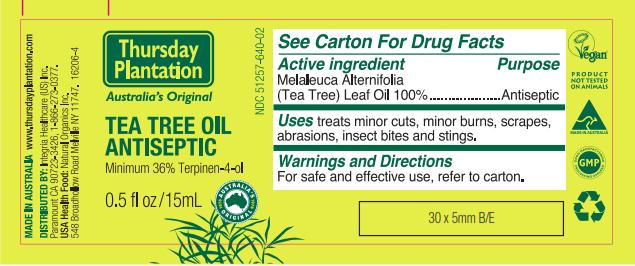 DRUG LABEL: Tea Tree Antiseptic
NDC: 51257-640 | Form: OIL
Manufacturer: Integria Healthcare US Inc.
Category: otc | Type: HUMAN OTC DRUG LABEL
Date: 20110317

ACTIVE INGREDIENTS: TEA TREE OIL 15 mL/15 mL

ACTIVE INGREDIENT

Melaleuca Alternifolia (Tea Tree) Leaf Oil 100%

PURPOSE

Antiseptic

INDICATIONS AND USAGE

treats minor cuts, minor burns, scrapes, abrasions, insect bites and stings.

WARNINGS

For external use only

- avoid contact with eyes, mouth, ears and other sensitive areas of the body
- if contact occurs, rinse thoroughly with water

Stop use and ask a doctor if condition worsens or does not improve within 7 days.

Keep out of reach of children

- if swallowed, get medical help or contact a Poison Control Center right away.

DOSAGE AND ADMINISTRATION

- apply to the affected area
- use sparingly by drop
- children under 12 years of age: consult a doctor

STORAGE AND HANDLING

store below 86 degrees F

PACKAGE LABEL

Tea Tree Oil Antiseptic

100% Pure

Minimum 36% Terpinen-4-ol

INACTIVE INGREDIENT

None.